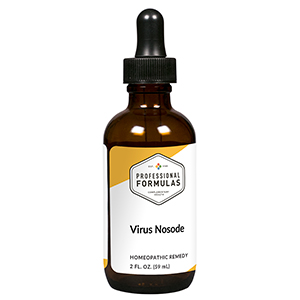 DRUG LABEL: Virus Nosode
NDC: 63083-4003 | Form: LIQUID
Manufacturer: Professional Complementary Health Formulas
Category: homeopathic | Type: HUMAN OTC DRUG LABEL
Date: 20190815

ACTIVE INGREDIENTS: BACILLUS CALMETTE-GUERIN LIVE ANTIGEN, UNSPECIFIED SUBSTRAIN 30 [hp_X]/59 mL; COXSACKIEVIRUS A21 30 [hp_X]/59 mL; HUMAN HERPESVIRUS 5 30 [hp_X]/59 mL; HUMAN HERPESVIRUS 4 30 [hp_X]/59 mL; HAEMOPHILUS INFLUENZAE 30 [hp_X]/59 mL; POLIOVIRUS TYPE 1 ANTIGEN (FORMALDEHYDE INACTIVATED) 30 [hp_X]/59 mL; DALEA FOLIOLOSA WHOLE 30 [hp_X]/59 mL; DRABA VERNA WHOLE 30 [hp_X]/59 mL; VACCINIA VIRUS STRAIN NEW YORK CITY BOARD OF HEALTH LIVE ANTIGEN 30 [hp_X]/59 mL; HUMAN VARICELLA-ZOSTER IMMUNE GLOBULIN 30 [hp_X]/59 mL
INACTIVE INGREDIENTS: ALCOHOL; WATER

N3

ACTIVE INGREDIENTS

all the following at 30X, 60X, 100X:
BCG
Coxsackievirus
Cytomegalovirus
Epstein-Barr virus
Haemophilus influenzae
Poliomyelitis
Roseola
Rubella
Vaccinotoxinum
Varicella

QUESTIONS

Professional Formulas

PO Box 2034 Lake Oswego, OR 97035

INDICATIONS

Temporarily relieves fatigue, sore throat, minor aches and pains in the muscles or joints, occasional headache, chills, sweats, cough, nausea or vomiting, or abdominal discomfort.*

PURPOSE

*Claims based on traditional homeopathic practice, not accepted medical evidence. Not FDA evaluated.

WARNINGS

Persistent symptoms may be a sign of a serious condition. If symptoms persist or are accompanied by a fever, rash, or persistent headache, consult a doctor. Keep out of the reach of children. In case of overdose, get medical help or contact a poison control center right away. If pregnant or breastfeeding, ask a healthcare professional before use.

Keep out of the reach of children.

PREGNANCY OR BREAST FEEDING

If pregnant or breastfeeding, ask a healthcare professional before use.

DIRECTIONS

Place drops under tongue 30 minutes before/after meals. Adults and children 12 years and over: Take 10 to 15 drops once weekly or monthly. If mild symptoms are present, take 10 drops up to 3 times per day. Consult a physician for use in children under 12 years of age.

OTHER INFORMATION

Tamper resistant. If seal is broken, do not use. After opening, close container tightly and store at room temperature away from heat.

INACTIVE INGREDIENTS

20% ethanol, purified water.

LABEL

Est 1985

Professional Formulas

Complementary Health

Virus Nosode

Homeopathic Remedy

2 FL. OZ. (59 mL)